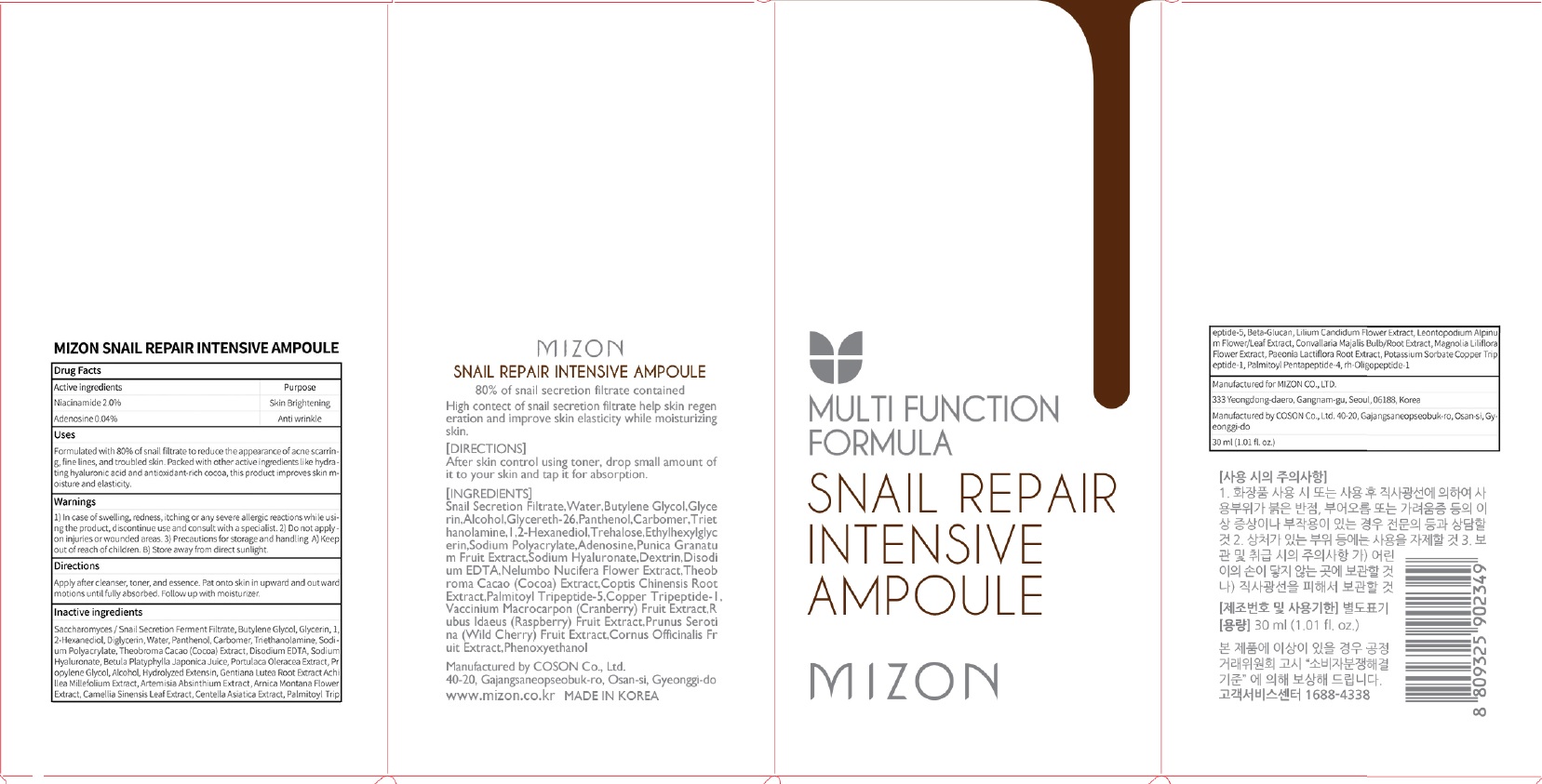 DRUG LABEL: MIZON SNAIL REPAIR INTENSIVE AMPOULE
NDC: 57718-240 | Form: LIQUID
Manufacturer: MIZON CO.,LTD.
Category: otc | Type: HUMAN OTC DRUG LABEL
Date: 20180723

ACTIVE INGREDIENTS: Niacinamide 0.60 g/30 mL; Adenosine 0.012 g/30 mL
INACTIVE INGREDIENTS: Butylene Glycol; Glycerin

ACTIVE INGREDIENT

Active ingredients: Niacinamide 2.0%, Adenosine 0.04%

INACTIVE INGREDIENT

Inactive ingredients:

Saccharomyces/Snail Secretion Ferment Filtrate, Butylene Glycol, Glycerin, 1,2-Hexanediol, Diglycerin, Water, Panthenol, Carbomer, Triethanolamine, Sodium Polyacrylate, Theobroma Cacao (Cocoa) Extract, Disodium EDTA, Sodium Hyaluronate, Betula Platyphylla Japonica Juice, Portulaca Oleracea Extract, Propylene Glycol, Alcohol, Hydrolyzed Extensin, Gentiana Lutea Root Extract, Achillea Millefolium Extract, Artemisia Absinthium Extract, Arnica Montana Flower Extract, Camellia Sinensis Leaf Extract, Centella Asiatica Extract, Palmitoyl Tripeptide-5, Beta-Glucan, Lilium Candidum Flower Extract, Leontopodium Alpinum Flower/Leaf Extract, Convallaria Majalis Bulb/Root Extract, Magnolia Liliflora Flower Extract, Paeonia Lactiflora Root Extract, Potassium Sorbate, Copper Tripeptide-1, Palmitoyl Pentapeptide-4, rh-Oligopeptide-1

PURPOSE

Purpose: Skin Brightening, Anti wrinkle

WARNINGS

1) In case of swelling, redness, itching or any severe allergic reactions while using the product, discontinue use and consult with a specialist. 2) Do not apply on injuries or wounded areas. 3) Precautions for storage and handling A) Keep out of reach of children. B) Store away from direct sunlight.

KEEP OUT OF REACH OF CHILDREN

Uses

Formulated with 80% of snail filtrate to reduce the appearance of acne scarring, fine lines, and troubled skin. Packed with other active ingredients like hydrating hyaluronic acid and antioxidant-rich cocoa, this product improves skin moisture and elasticity.

Directions

Apply after cleanser, toner, and essence. Pat onto skin in upward and outward motions until fully absorbed. Follow up with moisturizer.